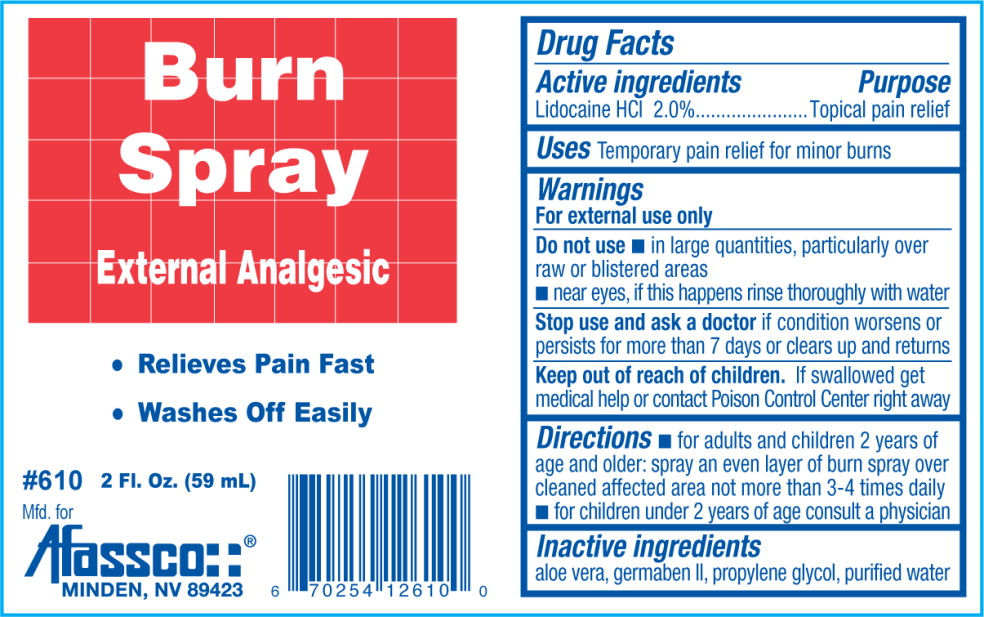 DRUG LABEL: Lidocaine Hydrochloride
NDC: 51532-6101 | Form: LIQUID
Manufacturer: Afassco Inc.
Category: otc | Type: HUMAN OTC DRUG LABEL
Date: 20120731

ACTIVE INGREDIENTS: Lidocaine Hydrochloride 200 mL/1 L
INACTIVE INGREDIENTS: aloe vera leaf; propylene glycol; diazolidinyl urea; water

Drug Facts

Active Ingredients

Lidocaine HCl 2.0%

Purpose

Topical pain relief

Uses

Temporary pain relief for minor burns

Warnings

For external use only

Do not use

- in large quantities, particularly over raw or blistered areas
- near eyes, if this happens rinse thoroughly with water

Stop use and ask doctor if condition worsens or persists for more than 7 days or clears up and returns

Keep out of reach of children.

If swallowed get medical help or contact a Poison Control Center right away

Directions

- for adults and children 2 years of age and older: spray an even layer of burn spray over cleaned affected area not more than 3-4 times daily
- for children under 2 years of age consult a physician

Inactive ingredients

aloe vera, germaben II, propylene glycol, purified water

PRINCIPAL DISPLAY PANEL – 2 oz. bottle

Burn
Spray
External Analgesic

- Relieves Pain Fast
- Washes Off Easily

#610 2 Fl. Oz. (59 mL)

Mfd. For
Afassco
MINDEN, NV 89423